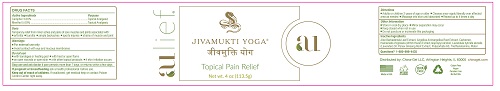 DRUG LABEL: China-Gel
NDC: 76305-402 | Form: CREAM
Manufacturer: China-Gel, Inc.
Category: otc | Type: HUMAN OTC DRUG LABEL
Date: 20251104

ACTIVE INGREDIENTS: MENTHOL 50 mg/1 g; CAMPHOR (SYNTHETIC) 30 mg/1 g
INACTIVE INGREDIENTS: ISOPROPYL ALCOHOL; LAVANDIN OIL; POLYSORBATE 60; HAMAMELIS VIRGINIANA LEAF; WATER; ANGELICA ARCHANGELICA ROOT; CARBOMER HOMOPOLYMER TYPE C (ALLYL PENTAERYTHRITOL CROSSLINKED); ASIAN GINSENG; ALOE VERA LEAF; TROLAMINE

China Gel - Jivamukti

Active Ingredients

Camphor 3.00%

Menthol 5.00%

Purpose

Topical Analgesic

Topical Analgesic

Uses

Temporary relief from minor aches and pains of sore muscles and joints associated with:

- arthritis
- bursitis
- simple backaches
- sports injuries
- strains of muscle and joint

Warnings

- For external use only
- Avoid contact with eye and mucous membranes

Do not use

- with bandages or heating pad
- with heat or open flame
- on open wounds or open skin
- with other topical products
- if skin irritation occurs

Stop use and ask doctor if

pain persists more than 7 days, or returns within a few days

If pregnant or breastfeeding

ask a health professional before use.

Keep out of reach of children.

If swallowed, get medical help or contact Poison Control Center right away.

Directions

- Adults or children 2 years or older
- Cleanse area-apply liberally over affected area as needed
- Massage into skin until absorbed
- Repeat up to 4 times a day

Other Information

- Store in cool dry place
- Minor separation may occur
- Keep closed when not in use
- Do not puncture or incinerate this packaging

Inactive Ingredients

Aloe Barbadensis Leaf Extract, Angelica Archangelica Root Extract, Carbomer, Hamamelis Virginiana (Witch Hazel) Extract, Isopropyl Alcohol, Lavandula hybrida abrialis (Lavender) Oil, Panax Gingseng Root Extract, Polysorbate 60, Triethanolmine, Water

Questions?

1-800-898-4435

Principal display panel

JIVAMUKTI YOGA

Topcial Pain Relief

Net wt. 4 oz (113.5g)